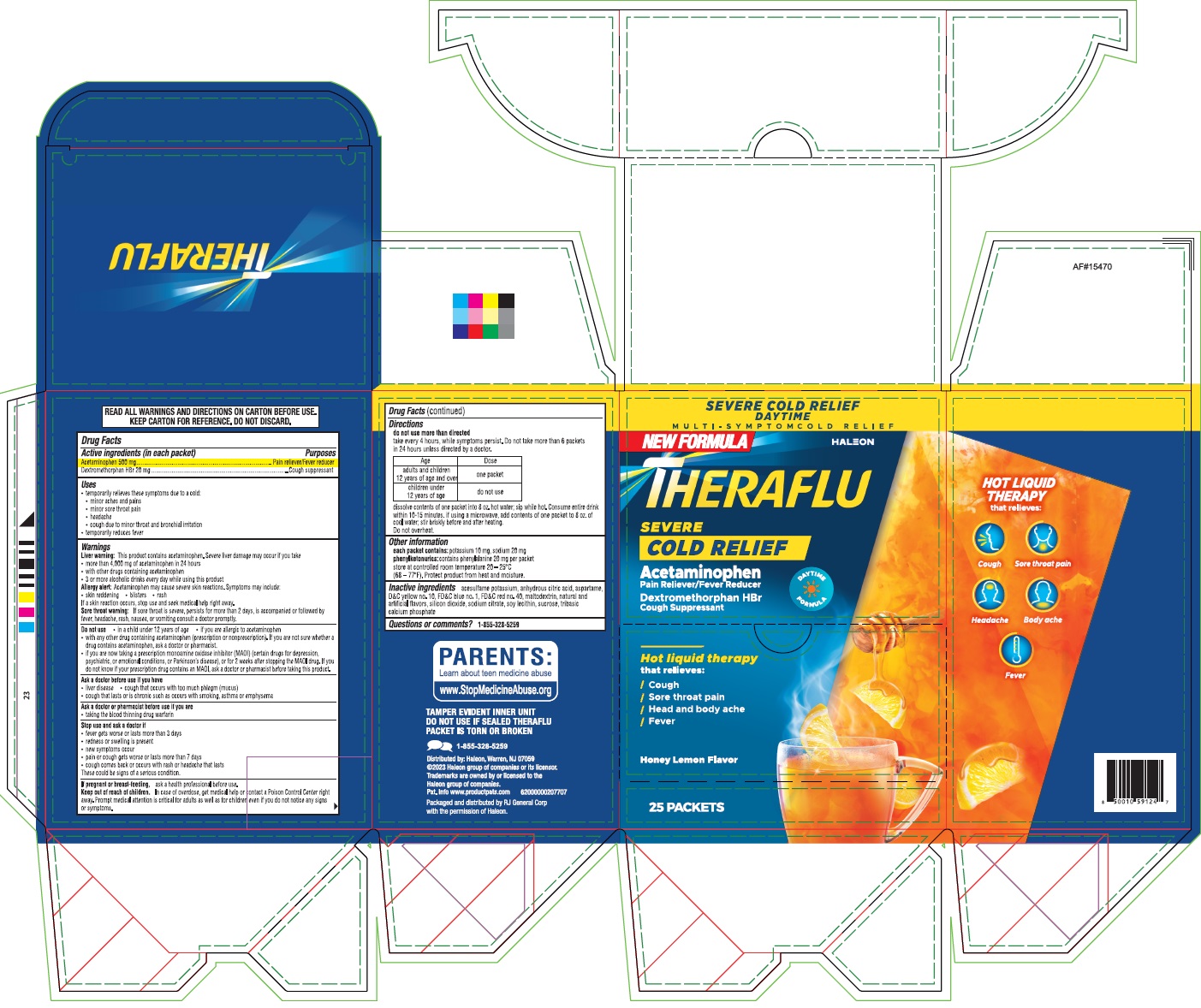 DRUG LABEL: Theraflu Severe Cold Relief Daytime
NDC: 70264-047 | Form: POWDER, FOR SOLUTION
Manufacturer: R J General Corporation
Category: otc | Type: HUMAN OTC DRUG LABEL
Date: 20251117

ACTIVE INGREDIENTS: ACETAMINOPHEN 500 mg/1 1; DEXTROMETHORPHAN HYDROBROMIDE 20 mg/1 1
INACTIVE INGREDIENTS: ACESULFAME POTASSIUM; ANHYDROUS CITRIC ACID; ASPARTAME; D&C YELLOW NO. 10; FD&C BLUE NO. 1; FD&C RED NO. 40; MALTODEXTRIN; SILICON DIOXIDE; SODIUM CITRATE, UNSPECIFIED FORM; LECITHIN, SOYBEAN; SUCROSE; TRIBASIC CALCIUM PHOSPHATE

THERAFLU
SEVERE COLD RELIEF
Acetaminophen
pain Reliever/Fever Reducer
Dextromethorphan HBr
Cough Suppressant

Active ingredients (in each packet)

Active ingredients (in each tablet) | Purpose
Acetaminophen 500 mg | Pain reliever/Fever reducer
Dextromethorphan HBr 20 mg | Cough Suppressant

Uses

- temporarily relieves these symptoms due to a cold:
  - minor aches and pains
  - minor sore throat pain
  - headache
  - cough due to minor throat and bronchial irritation
- temporarily reduces fever

Warnings

Liver warning:This product contains acetaminophen. Severe liver damage may occur if you take

- more than 4,000 mg of acetaminophen in 24 hours
- with other drugs containing acetaminophen
- 3 or more alcoholic drinks every day while using this product

Allergy alert:Acetaminophen may cause severe skin reactions. Symptoms may include:

- skin reddening
- blisters
- rash

If a skin reaction occurs, stop use and seek medical help right away.

Sore throat warning:If sore throat is severe, persists for more than 2 days, is accompanied or followed by fever, headache, rash, nausea, or vomiting consult a doctor promptly.

Do not use

- in a child under 12 years of age
- if you are allergic to acetaminophen
- with any other drug containing acetaminophen (prescription or nonprescription). If you are not sure whether a drug contains acetaminophen, ask a doctor or a pharmacist.
- if you are now taking a prescription monoamine oxidase inhibitor (MAOI) (certain drugs for depression, psychiatric, or emotional conditions, or Parkinson's disease), or for 2 weeks after stopping the MAOI drug. If you do not know if your prescription drug contains an MAOI, ask a doctor or pharmacist before taking this product.

Ask doctor before use if you have

- liver disease
- cough that occurs with too much phlegm (mucus)
- cough that lasts or is chronic such as occurs with smoking, asthma or emphysema

Ask a doctor or pharmacist before use if you are

- taking the blood thinning drug warfarin

Stop use and ask a doctor if

- fever gets worse or lasts more than 3 days
- redness or swelling is present
- new symptoms occur
- pain, cough or nasal congestion gets worse or lasts more than 7 days
- cough comes back or occurs with rash or headache that lasts
  These could be signs of a serious condition.

PREGNANCY OR BREAST FEEDING

If pregnant or breast-feeding,ask a health professional before use.

Keep out of reach of children.In case of overdose, get medical help or contact a Poison Control Center right away. Prompt medical attention is critical for adults as well as for children even if you do not notice any signs or symptoms.

Directions

- do not use more than directed
- take every 4 hours, while symptoms persist. Do not take more than 6 packets in 24 hours unless directed by a doctor.

Age | Dose
adults and children; 12 years of age and over | one packet
children under; 12 years of age | do not use

- dissolve contents of one packet into 8 oz. hot water; sip while hot. Consume entire drink within 10-15 minutes. if using a microwave, add contents of one packet to 8 oz. of cool water; stir briskly before and after heating.
- Do not overheat.

Other information

- each packet contains:potassium 10 mg, sodium 20 mg
- phenylketonurics:contains phenylalanine 20 mg per packet
- store at controlled room temperature 20o-25oC (68o- 77oF). Protect product from heat and moisture.

Inactive ingredients

acesulfame potassium, anhydrous citric acid, aspartame, D&C yellow no.10, FD&C blue no. 1, FD&C red no. 40, maltodextrin, natural and artificial flavors, silicon dioxide, sodium citrate, soy lecithin, sucrose, tribasic calcium phosphate

Questions or comments?

1-855-328-5259

PRINCIPAL DISPLAY PANEL

THERAFLU SEVERE COLD RELIEF - Acetaminophen, Dextromethorphan HBr - NDC 70264-047-01 - 25s Packets Caton Label